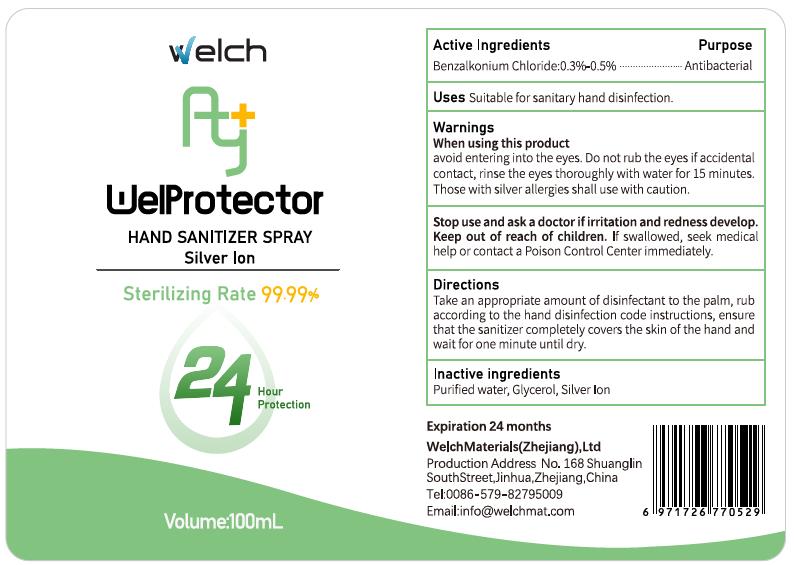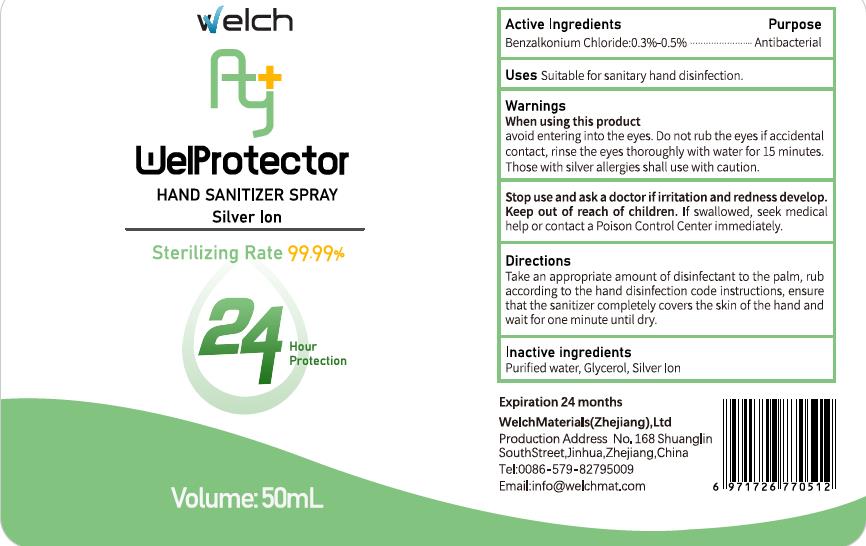 DRUG LABEL: Hand sanitizer
NDC: 81242-001 | Form: SPRAY
Manufacturer: Welch Materials (Zhejiang), Inc.
Category: otc | Type: HUMAN OTC DRUG LABEL
Date: 20201221

ACTIVE INGREDIENTS: BENZALKONIUM CHLORIDE 0.3 g/100 mL
INACTIVE INGREDIENTS: WATER; SILVER CHLORIDE; GLYCERIN

yuexu 0.13% BENZALKONIUM CHLORIDE

Directions

Take an appropriate amount of disinfectant to the palm, rub according to the hand disinfection code instructions, ensure that the sanitizer completely covers the skin of the hand sand wait for one minute until dry

Active Ingredient

Benzalkonium Chloride 0.3%

Purpose

Antibacterial

USE

Suitable for sanitary hand disinfection.

Warning

When using this product, avoid entering into the eyes.

Do not rub the eyes if accidental contact, rinse the eyes thoroughly with water for 15 minutes.

Those with silver allergies shall use with caution.

Keep out of reach of children.

If swallowed, seek medical help or contact a Poison Control Center immediately.

Inactive ingredients

Purified water, Glycerol, Silver Ion

PACKAGE LABEL

50 ml NDC 81242-001-01 100ml NDC 81242-001-02